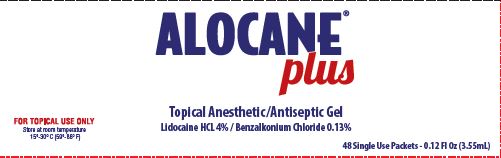 DRUG LABEL: Alocane Plus
NDC: 68229-300 | Form: GEL
Manufacturer: Quest Products LLC
Category: otc | Type: HUMAN OTC DRUG LABEL
Date: 20251204

ACTIVE INGREDIENTS: LIDOCAINE HYDROCHLORIDE 4 g/100 mL; BENZALKONIUM CHLORIDE 0.13 g/100 mL
INACTIVE INGREDIENTS: PROPANEDIOL; ALOE VERA LEAF; DIMETHYL ISOSORBIDE; HYDROXYETHYL CELLULOSE (5500 MPA.S AT 2%); PHENOXYETHANOL; CAPRYLYL GLYCOL; CHLORPHENESIN; .ALPHA.-TOCOPHEROL ACETATE; WATER

Alocane® Plus

Drug Facts

ACTIVE INGREDIENT

Active Ingredient | Purpose
Benzalkonium Chloride 0.13%; Lidocaine HCL 4% | First Aid Antiseptic; Topical Analgesic

Uses:

First aid to help prevent bacterial infection associated with contamination of the skin. Temporarily relieves pain and itching due to:

- Minor Burns
- Minor Cuts & Scrapes
- Minor Skin Irritations

Warnings

For external use only. Avoid contact with eyes.

Keep out of reach of children. In case of accidental ingestion, seek medical help or call a Poison Control Center right away.

Stop use and ask doctor: if condition worsens, or if symptoms persist for more than 7 days or clear up and occur again within a few days.

PREGNANCY OR BREAST FEEDING

If pregnant or breast-feeding, ask a health care professional before use.

Directions

Adults and children 2 years of age and older: Apply to affected areas not more than 3 to 4 times daily.

Children under 2 years of age: consult a doctor.

Other Information

Store at room temperature 15°-30°C (59°-86°F)

Inactive Ingredients

1,3-Propanediol, Aloe Barbadensis (Aloe) Leaf Juice, Caprylyl Glycol, Chlorphenesin, Dimethyl Isosorbide, Hydroxyethyl Cellulose, Phenoxyethanol, Tocopheryl Acetate (Vitamin E), Water.